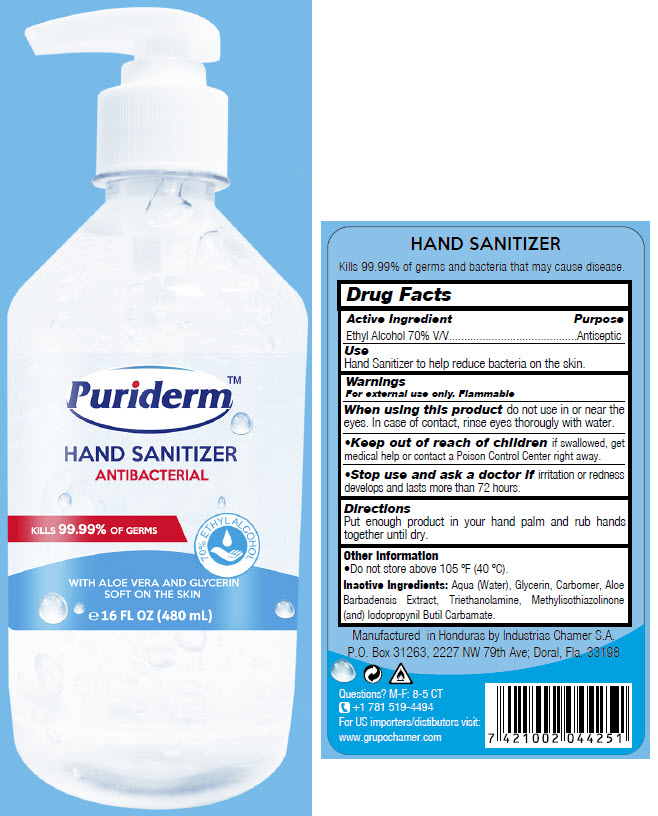 DRUG LABEL: Hand Sanitizer
NDC: 51774-001 | Form: GEL
Manufacturer: Industrias Chamer Sa De Cv
Category: otc | Type: HUMAN OTC DRUG LABEL
Date: 20210107

ACTIVE INGREDIENTS: Alcohol 70 mL/100 mL
INACTIVE INGREDIENTS: WATER; GLYCERIN; CARBOMER HOMOPOLYMER, UNSPECIFIED TYPE; ALOE VERA LEAF; TROLAMINE; METHYLISOTHIAZOLINONE; IODOPROPYNYL BUTYLCARBAMATE

Puriderm™ HAND SANITIZER

Drug Facts

Active Ingredient

Ethyl Alcohol 70% V/V

Purpose

Antiseptic

Use

Hand Sanitizer to help reduce bacteria on the skin.

Warnings

For external use only. Flammable

When using this product do not use in or near the eyes. In case of contact, rinse eyes thorougly with water.

- Keep out of reach of children if swallowed, get medical help or contact a Poison Control Center right away.

- Stop use and ask a doctor if irritation or redness develops and lasts more than 72 hours.

Directions

Put enough product in your hand palm and rub hands together until dry.

Other Information

- Do not store above 105 ºF (40 ºC).

Inactive Ingredients

Aqua (Water), Glycerin, Carbomer, Aloe Barbadensis Extract, Triethanolamine, Methylisothiazolinone (and) Iodopropynil Butil Carbamate.

Questions?

M-F: 8-5 CT

+1 781 519-4494

Manufactured in Honduras by Industrias Chamer S.A.
P.O. Box 31263, 2227 NW 79th Ave; Doral, Fla. 33198

PRINCIPAL DISPLAY PANEL - 480 mL Bottle Label

Puriderm™

HAND SANITIZER
ANTIBACTERIAL

KILLS 99.99% OF GERMS

70% ETHYL ALCOHOL

WITH ALOE VERA AND GLYCERIN
SOFT ON THE SKIN

℮ 16 FL OZ (480 mL)